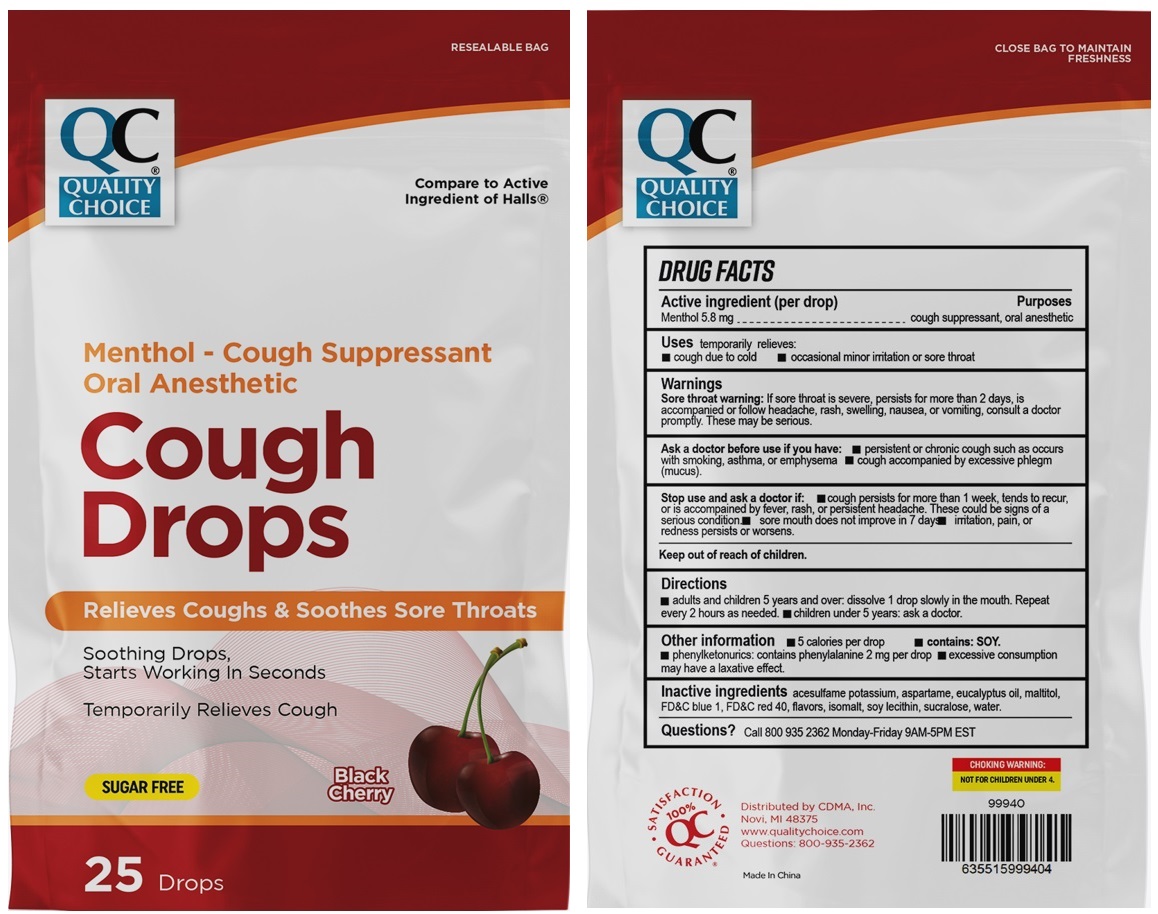 DRUG LABEL: QUALITY CHOICE Cough Drops Black Cherry SUGAR FREE
NDC: 83698-624 | Form: LOZENGE
Manufacturer: Xiamen Kang Zhongyuan Biotechnology Co., Ltd.
Category: otc | Type: HUMAN OTC DRUG LABEL
Date: 20251229

ACTIVE INGREDIENTS: MENTHOL, UNSPECIFIED FORM 5.8 mg/1 1
INACTIVE INGREDIENTS: ACESULFAME POTASSIUM; ASPARTAME; EUCALYPTUS OIL; MALTITOL; FD&C BLUE NO. 1; FD&C RED NO. 40; ISOMALT; SOYBEAN LECITHIN; SUCRALOSE; WATER

QUALITY CHOICE®Cough Drops Black Cherry

Active ingredient (per drop)

Menthol 5.8 mg

Purposes

cough suppressant, oral anesthetic

Uses

temporarily relieves:
• cough due to cold • occasional minor irritation or sore throat

Warnings

Sore throat warning:If sore throat is severe, persists for more than 2 days, is accompanied or follow headache, rash, swelling, nausea, or vomiting, consult a doctor promptly. These may be serious.

Ask a doctor before use if you have:• persistent or chronic cough such as occurs with smoking, asthma, or emphysema • cough accompanied by excessive phlegm (mucus).

Stop use and ask a doctor if:• cough persists for more than 1 week, tends to recur, or is accompanied by fever, rash, or persistent headache. These could be signs of a serious condition. • sore mouth does not improve in 7 days • irritation, pain, or redness persists or worsens.

Keep out of reach of children.

Directions

• adults and children 5 years and over: dissolve 1 drop slowly in the mouth. Repeat every 2 hours as needed. • children under 5 years: ask a doctor.

Other information

• 5 calories per drop • contains: SOY.• phenylketonurics: contains phenylalanine 2 mg per drop • excessive consumption may have a laxative effect.

Inactive ingredients

acesulfame potassium, aspartame, eucalyptus oil, maltitol, FD&C blue 1, FD&C red 40, flavors, isomalt, soy lecithin, sucralose, water.

Questions?

Call 800 935 2362 Monday-Friday 9AM-5PM EST

RESEALABLE BAG

Compare to Active Ingredient of Halls®

Relieves Coughs & Soothes Sore Throats

Soothing Drops,
Starts Working In Seconds

Temporarily Relieves Cough

CLOSE BAG TO MAINTAIN FRESHNESS

CHOKING WARNING:
NOT FOR CHILDREN UNDER 4.

QC 100% SATISFACTION GUARANTEED ®

Distributed by CDMA, Inc.
Novi, MI 48375
www.qualitychoice.com
Questions: 800-935-2362

Made In China